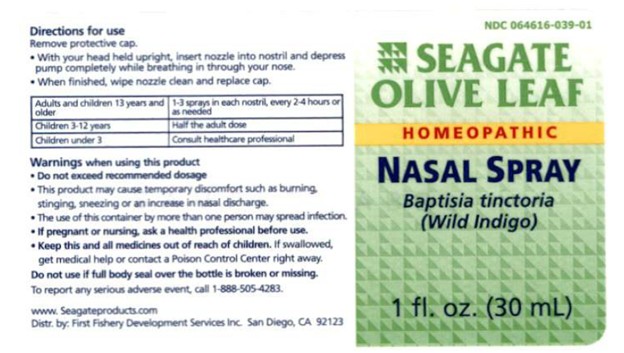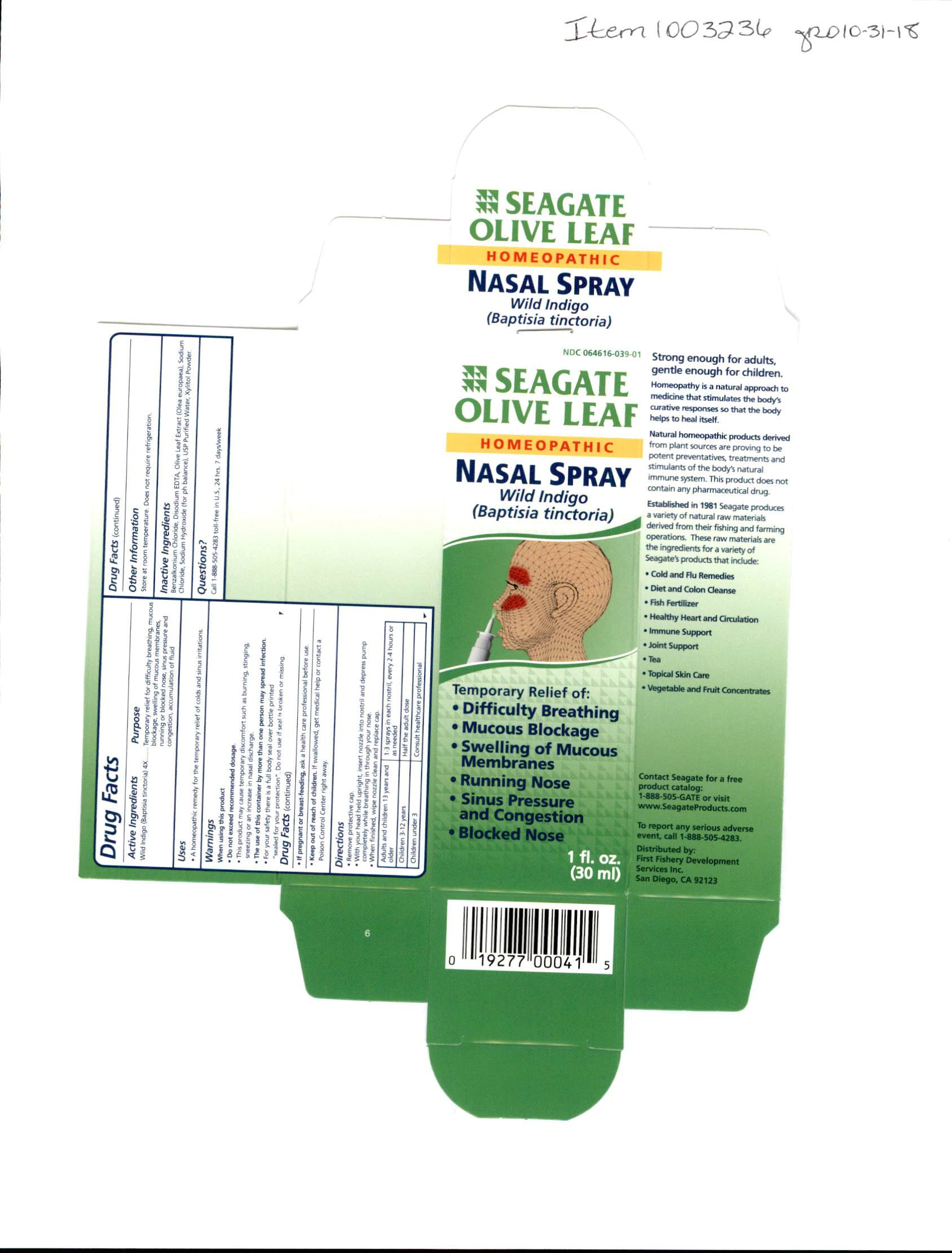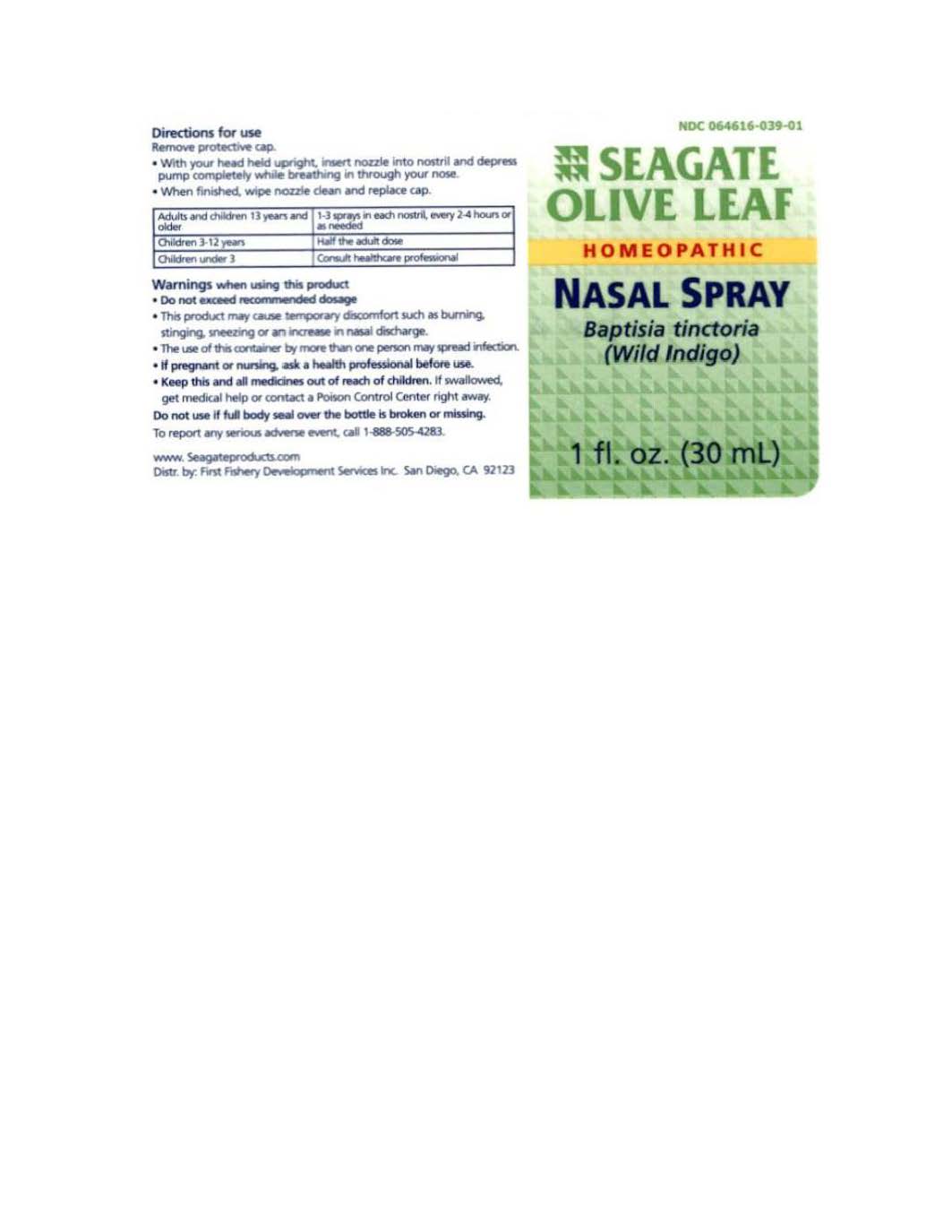 DRUG LABEL: Olive Leaf Nasal
NDC: 64616-039 | Form: SPRAY
Manufacturer: Vitality Works, Inc.
Category: homeopathic | Type: HUMAN OTC DRUG LABEL
Date: 20251217

ACTIVE INGREDIENTS: BAPTISIA TINCTORIA 4 [hp_X]/1 mL
INACTIVE INGREDIENTS: BENZALKONIUM CHLORIDE; WATER; SODIUM CHLORIDE; XYLITOL; SODIUM HYDROXIDE; COBALT DISODIUM EDETATE; OLEA EUROPAEA LEAF

Olive Leaf Nasal Spray

Olive Leaf Nasal Spray

Wild Indigo (Baptisia tinctoria) 4X

Olive Leaf Nasal Spray

Benzalkonium Chloride, Olive Leaf Extract (Olea Europaea), Sodium Chloride, Sodium Hydroxide (for pH balance), USP Purified Water, Xylitol Powder.

Olive Leaf Nasal Spray

Do not exceed recommended dosage. This product may cause temporary discomfort such as burning, stinging, sneezing or an increase in nasal doscharge. The use of this container by more than one person my spread infection. For your safety there is a full body seal over bottle printed "sealed for your protection". Do not use if seal is broken or missing. If pregnant or breastfeeding ask a health care professional before use.

Olive Leaf Nasal Spray

Keep this and all medicines out of reach of children.

Olive Leaf Nasal Spray

A homeopathic remedy for the temporary relief of cold and sinus irritations.

Olive Leaf Nasal Spray

Remove the protective cap. With your head held upright insert nozzel into nostril and depress pump completely while breathing in through your nose. When finished, wipe nozzel clean and replace cap.

Adults and children 13 years and older, use 1-3 sprays in each nostril every 2-4 hours or as needed. Children 3-12 years, half the adult dosage. children under 3 years of age, consult a health care professional.

Olive Leaf Nasal Spray

Baptisia tinctoria - Temporary Relief for diificulty breathing, mucous blockage, swelling of mucous membranes, running or blocked nose, sinus pressure and congestion, accumulation of fluid.

QUESTIONS

To report any serious adverse event, call 1-888-505-4283.

www.seagteproducts.com

Distributed by:

Fishery Fishery Development Services Inc. San Diego, CA 92123